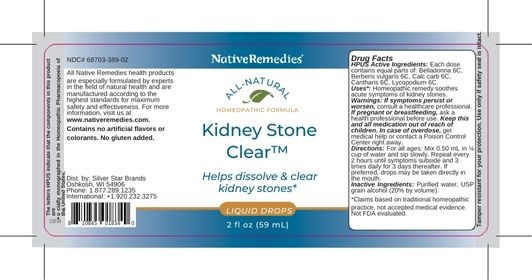 DRUG LABEL: NativeRemedies Kidney Stone Clear
NDC: 68703-389 | Form: LIQUID
Manufacturer: Silver Star Brands
Category: homeopathic | Type: HUMAN OTC DRUG LABEL
Date: 20250101

ACTIVE INGREDIENTS: LYCOPODIUM CLAVATUM SPORE 6 [hp_C]/59 mL; OYSTER SHELL CALCIUM CARBONATE, CRUDE 6 [hp_C]/59 mL; LYTTA VESICATORIA 6 [hp_C]/59 mL; ATROPA BELLADONNA 6 [hp_C]/59 mL; BERBERIS VULGARIS FRUIT 6 [hp_C]/59 mL
INACTIVE INGREDIENTS: WATER; ALCOHOL

NativeRemedies® Kidney Stone Clear™

HPUS Active ingredients: Each dose contains equal parts of: Belladonna 6C, Berberis vulgaris 6C, Calc carb 6C, Cantharis 6C, Lycopodium 6C.

The letters HPUS indicate that the components in this product are officially monographed in the Homeopathic Pharmacopoeia of the United States.

Uses*

Uses*: Homeopathic remedy soothes acute symptoms of kidney stones.

*Claims based on traditional homeopathic practice, not accepted medical evidence. Not FDA evaluated.

Warnings

Warings: If symptoms persist or worsen, consult a healthcare professional. If pregnant or breastfeeding, ask a health professional before use. Keep this and all medication out of reach of children. In case of overdose, get medical help or contact a Poison Control Center right away.

Directions

Directions: For all ages: Mix 0.50 mL in 1/4 cup water and sip slowly. Repeat every 2 hours until symptoms subside and 3 times daily for 3 days thereafter. If preferred, dorps may be taken directly in the mouth.

OTHER SAFETY INFORMATION

Contains no artificial flavors or colorants. No gluten added.

Tamper resistant for your protection. Use only if safety seal is intact.

Inactive Ingredients

Inactive Ingredients: Purified water, USP grain alcohol (20% by volumn).

KEEP OUT OF REACH OF CHILDREN

Keep this and all medication out of reach of children. In case of overdose, get medical help or contact a Poison Control Center right away.

PREGNANCY OR BREAST FEEDING

If pregnant or breastfeeding, ask a health professional before use.

PURPOSE

Helps dissolve & clear kidney stones.